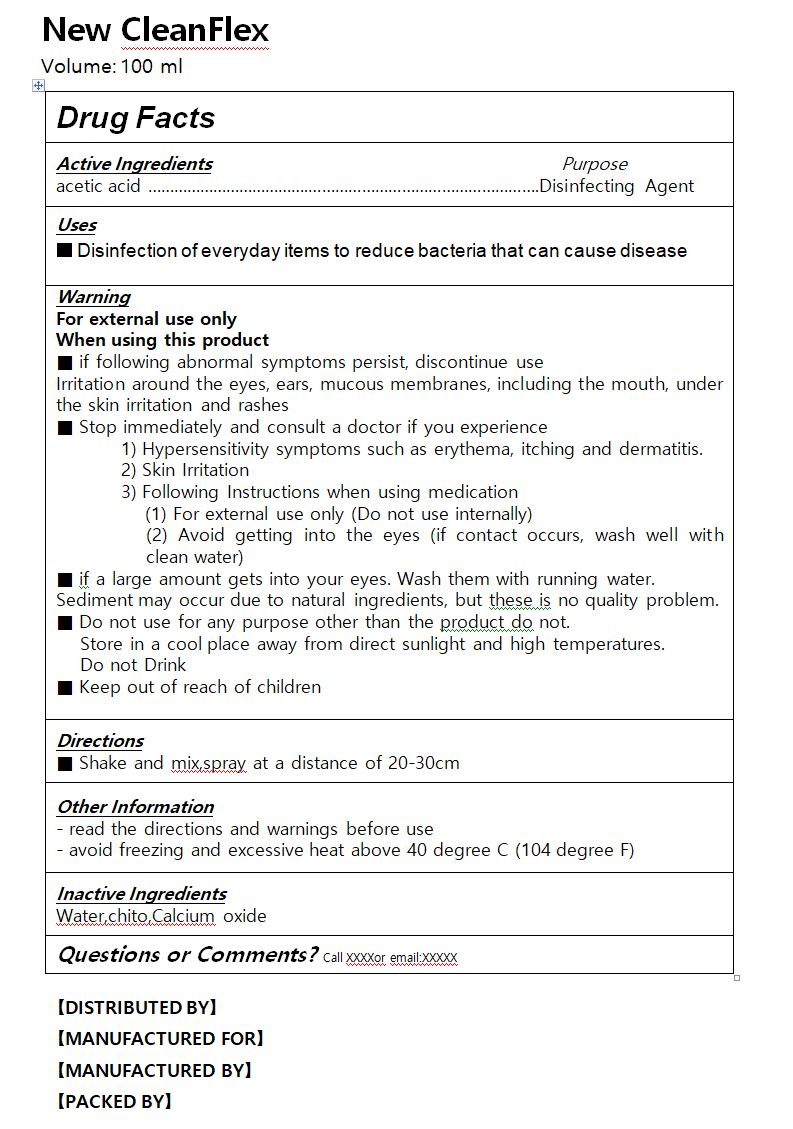 DRUG LABEL: New CleanFlex
NDC: 81463-0002 | Form: LIQUID
Manufacturer: D.O Bio
Category: otc | Type: HUMAN OTC DRUG LABEL
Date: 20211224

ACTIVE INGREDIENTS: ACETIC ACID 1.5 g/100 mL
INACTIVE INGREDIENTS: WATER

Drug Facts

ACTIVE INGREDIENT

acetic acid

PURPOSE

sterilization, disinfection

KEEP OUT OF REACH OF THE CHILDREN

INDICATIONS AND USAGE

take appropriate amount where needed

WARNINGS

■ Flammable. Keep away from fire or flame.

■ For external use only.

■ Do not use in eyes.

■ lf swallowed, get medical help promptly.

■ Stop use, ask doctor lf irritation occurs.

■ Keep out of reach of children.

DOSAGE AND ADMINISTRATION

for external use only

INACTIVE INGREDIENT

Water,chito,Calcium oxide